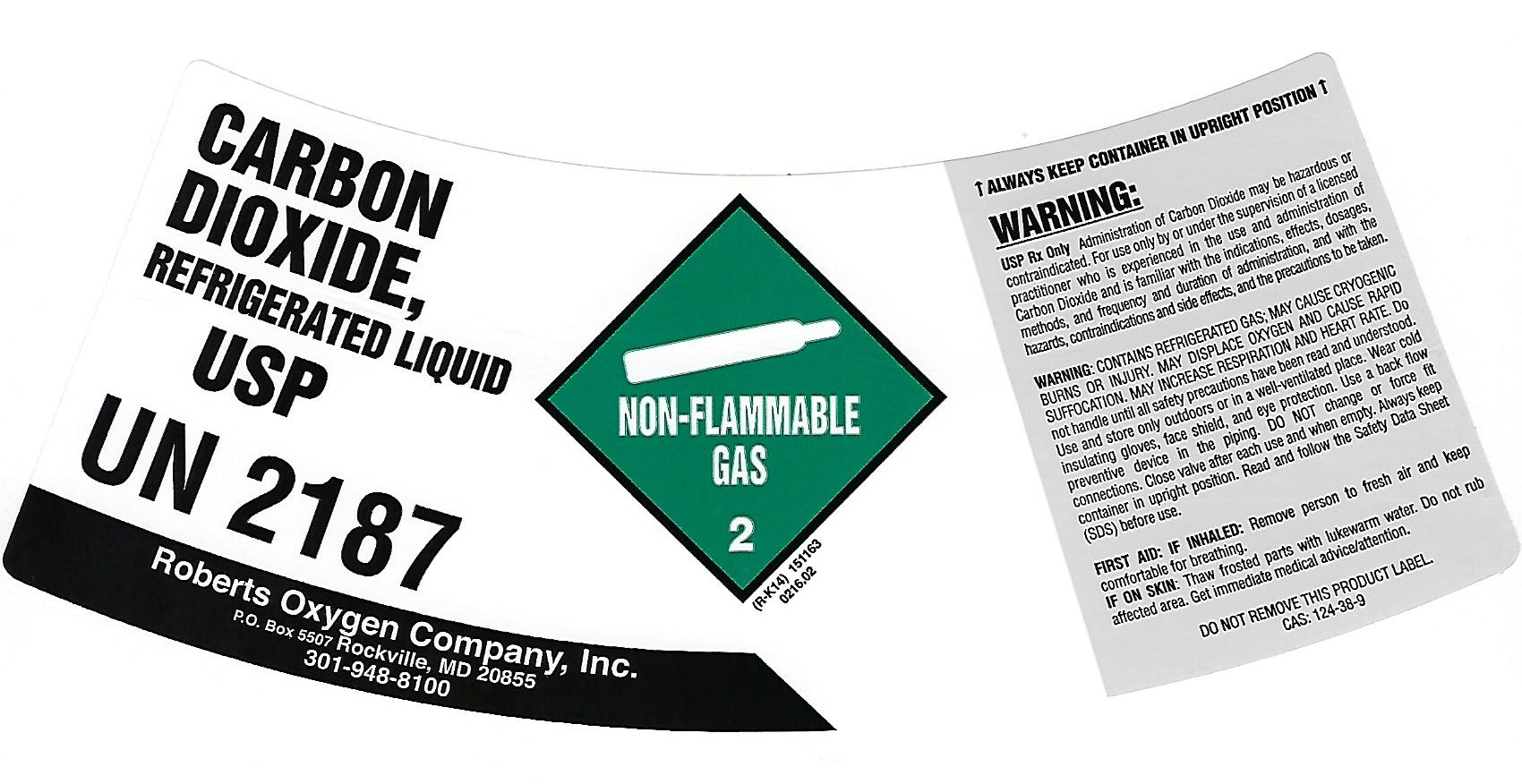 DRUG LABEL: Carbon Dioxide
NDC: 46123-240 | Form: GAS
Manufacturer: Roberts Oxygen Company, Inc.
Category: prescription | Type: HUMAN PRESCRIPTION DRUG LABEL
Date: 20251117

ACTIVE INGREDIENTS: CARBON DIOXIDE 990 mL/1 L

CARBON DIOXIDE, LIQUID USP - 240

PACKAGE LABEL

CARBON
DIOXIDE,
REFRIGERATED LIQUID
USP
UN2187
NON-FLAMMABLE GAS 2
Roberts Oxygen Company, Inc.
PO BOX 5507 Rockville, MD 20855
301-948-8100
↑ALWAYS KEEP CONTAINER IN UPRIGHT POSITION↑

WARNING:
USP Rx ONLY. Administration of Carbon Dioxide USP may be hazardous or contraindicated. For use only by or under the supervision of a licensed practitioner who is experienced in the use and administration of Carbon Dioxide USP and is familiar with the indications, effects, dosages, methods, and frequency and duration of administration, and the hazards, contraindications and side effects and the precautions to be taken.
WARNING: CONTAINS REFRIGERATED GAS; MAY CAUSE CRYOGENIC BURNS OR INJURY. MAY DISPLACE OXYGEN AND CAUSE RAPID SUFFOCATION. MAY INCREASE RESPIRATION AND HEART RATE. Do not handle until all safety precautions have been read and understood. Use and store only outdoors or in a well-ventilated place. Wear cold insulating gloves, face shield, and eye protection. Use a back flow preventative device in the piping. DO NOT change or force fit connections. Close valve after each use and when empty. Always keep container in upright position. Read and follow the Safety Data Sheet (SDS) before use.

FIRST AID: IF INHALED:Remove person to fresh air and keep comfortable for breathing.
IF ON SKIN:Thaw frosted parts with lukewarm water. Do not rub affected area. Get immediate medical advice/attention.
DO NOT REMOVE THIS PRODUCT LABEL
CAS: 124-38-9